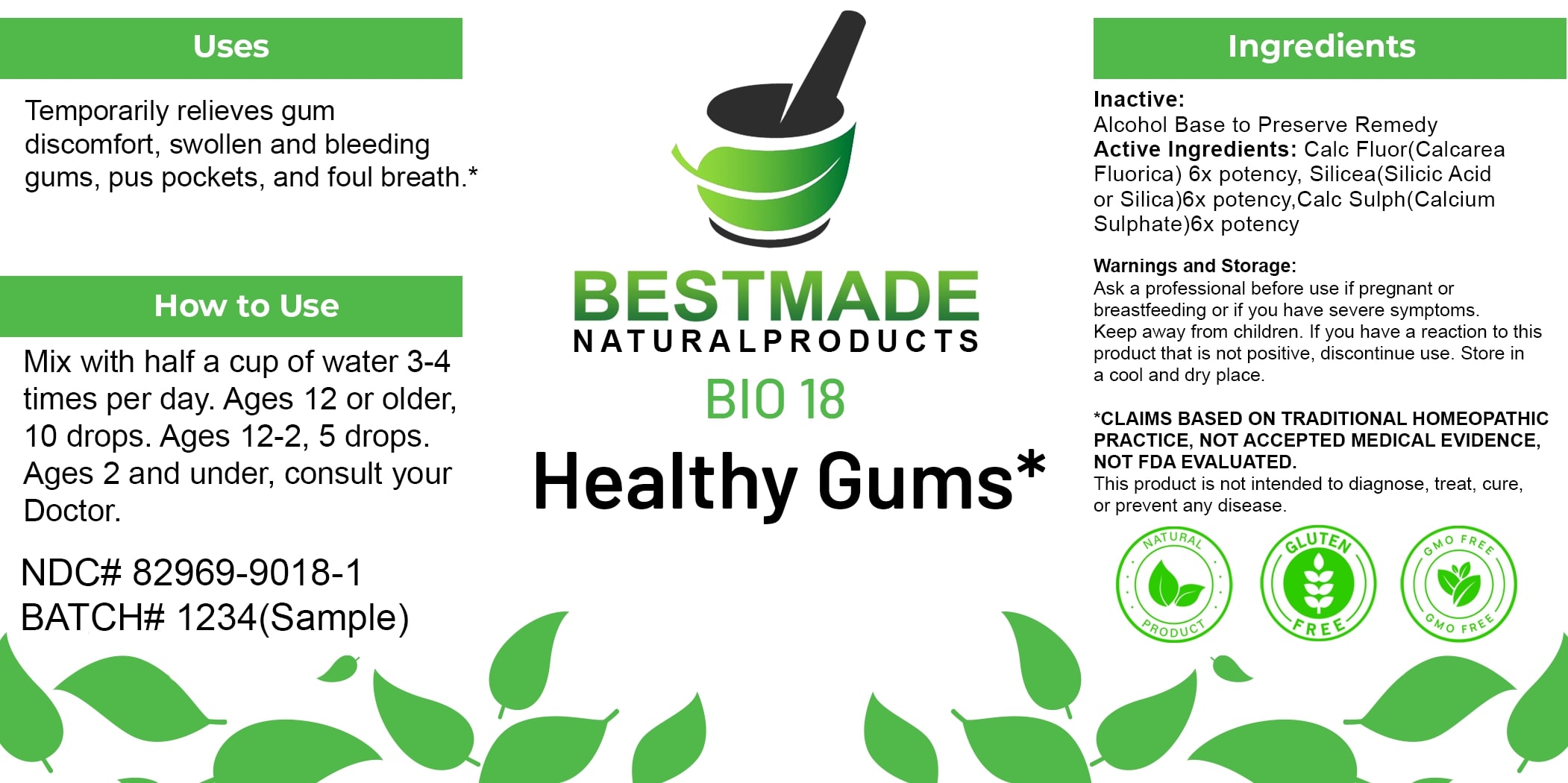 DRUG LABEL: Bestmade Natural Products BIO18
NDC: 82969-9018 | Form: LIQUID
Manufacturer: Bestmade Natural Products
Category: homeopathic | Type: HUMAN OTC DRUG LABEL
Date: 20250311

ACTIVE INGREDIENTS: CALCIUM SULFATE ANHYDROUS 6 [hp_X]/6 [hp_X]; CALCIUM FLUORIDE 6 [hp_X]/6 [hp_X]; SILICA 6 [hp_X]/6 [hp_X]
INACTIVE INGREDIENTS: ALCOHOL 6 [hp_X]/6 [hp_X]

BIO 18 Healthy Gums*

DOSAGE AND ADMINISTRATION

How to Use

Mix with half a cup of water 3-4 times per day. Ages 12 or older, 10 drops. Ages 12-2, 5 drops. Ages 2 and under, consult your Doctor.

INACTIVE INGREDIENT

Ingredients

Inactive: Alcohol Base to Preserve Remedy

ACTIVE INGREDIENT

Active Ingredients: Calc Fluor (Calcarea Fluorica) 6x potency, Silicea (Silicic Acid or Silica) 6x potency, Calc Sulph (Calcium Sulphate) 6x potency

Uses

Temporarily relieves gum discomfort, swollen and bleeding gums, pus pockets, and foul breath.*

*CLAIMS BASED ON TRADITIONAL HOMEOPATHIC PRACTICE, NOT ACCEPTED MEDICAL EVIDENCE, NOT FDA EVALUATED.

This product is not intended to diagnose, treat, cure, or prevent any disease.

Uses

Temporarily relieves gum discomfort, swollen and bleeding gums, pus pockets, and foul breath.*

*CLAIMS BASED ON TRADITIONAL HOMEOPATHIC PRACTICE, NOT ACCEPTED MEDICAL EVIDENCE, NOT FDA EVALUATED.

This product is not intended to diagnose, treat, cure, or prevent any disease.

KEEP OUT OF REACH OF CHILDREN

Warnings and Storage:

Ask a professional before use if pregnant or breastfeeding or if you have severe symptoms. Keep away from children. If you have a reaction to this product that is not positive, discontinue use. Store in a cool and dry place.

Warnings and Storage:

Ask a professional before use if pregnant or breastfeeding or if you have severe symptoms. Keep away from children. If you have a reaction to this product that is not positive, discontinue use. Store in a cool and dry place.

*CLAIMS BASED ON TRADITIONAL HOMEOPATHIC PRACTICE, NOT ACCEPTED MEDICAL EVIDENCE, NOT FDA EVALUATED.

This product is not intended to diagnose, treat, cure, or prevent any disease.

Entire package label